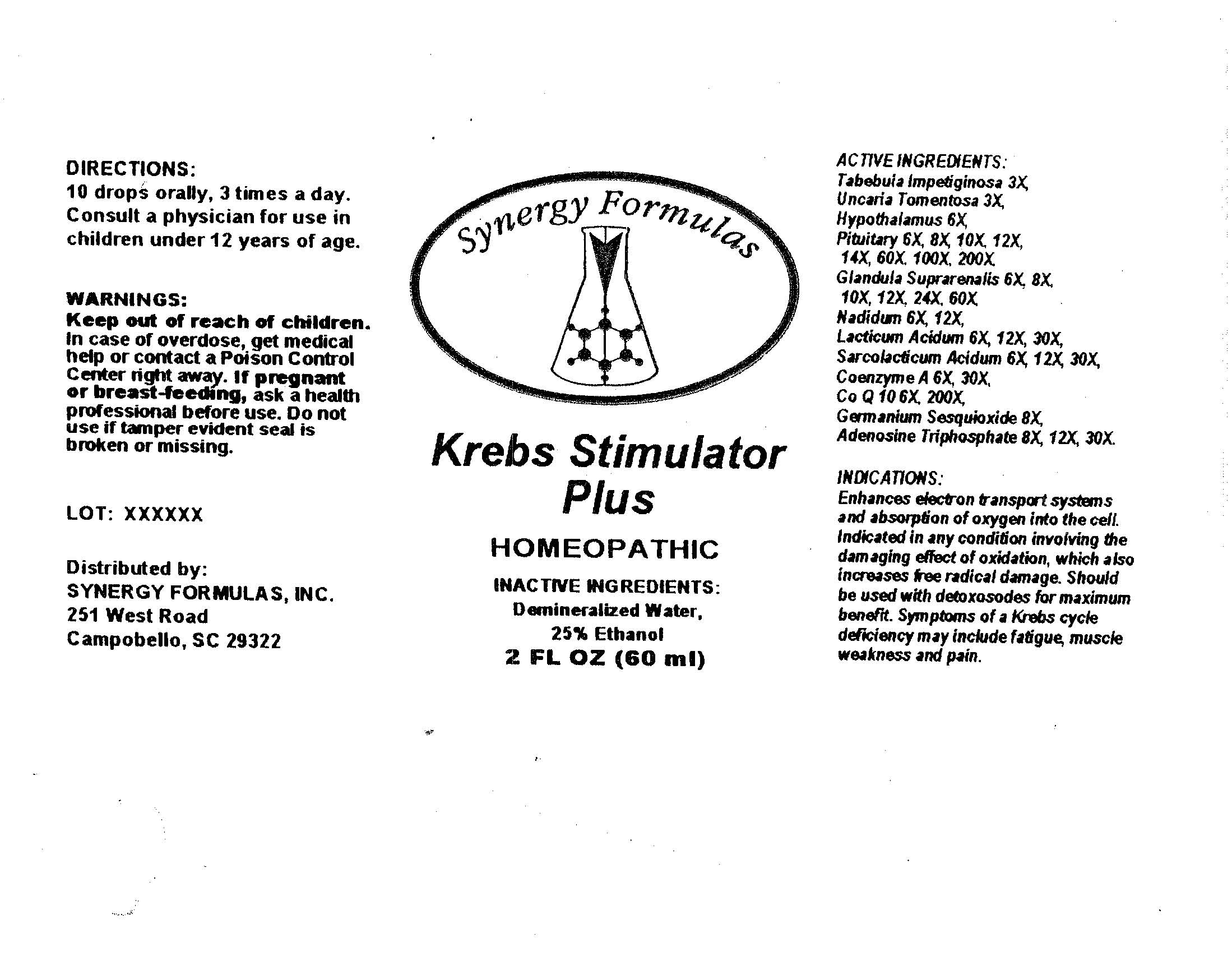 DRUG LABEL: Krebs Stimulator Plus
NDC: 57520-0217 | Form: LIQUID
Manufacturer: Apotheca Company
Category: homeopathic | Type: HUMAN OTC DRUG LABEL
Date: 20100719

ACTIVE INGREDIENTS: TABEBUIA IMPETIGINOSA BARK 3 [hp_X]/1 mL; CAT'S CLAW 3 [hp_X]/1 mL; SUS SCROFA HYPOTHALAMUS 6 [hp_X]/1 mL; SUS SCROFA PITUITARY GLAND 200 [hp_X]/1 mL; SUS SCROFA ADRENAL GLAND 60 [hp_X]/1 mL; NADIDE 12 [hp_X]/1 mL; LACTIC ACID, DL- 30 [hp_X]/1 mL; LACTIC ACID, L- 30 [hp_X]/1 mL; COENZYME A 30 [hp_X]/1 mL; ADENOSINE TRIPHOSPHATE 30 [hp_X]/1 mL; BIS(CARBOXYETHYL)GERMANIUM SESQUIOXIDE 8 [hp_X]/1 mL; UBIDECARENONE 200 [hp_X]/1 mL
INACTIVE INGREDIENTS: WATER; ALCOHOL

Krebs Stimulator Plus

ACTIVE INGREDIENT

ACTIVE INGREDIENTS: Tabebuia impetiginosa 3X, Uncaria tomemtosa 3X, Hypothalamus 6X, Pituitary 6X, 8X, 10X, 12X, 14X, 60X, 100X, 200X, Glandula suprarenalis 6X, 8X, 10X, 12X, 24X, 60X, Nadidum 6X, 12X, Lacticum acidum 6X, 12X, 30X, Sarcolacticum acidum 6X, 12X, 30X, Coenzyme A 6X, 30X, Co Q 10 6X, 200X, Germanium Sesquioxide 8X, Adenosine triphosphate 8X, 12X, 30X.

PURPOSE

INDICATIONS: Enhances electron transport systems and absorption of oxygen into the cell. Indicated in any condition involving the damaging effect of oxidation, which also increases free radical damage. Should be used with detoxosodes for maximum benefit. Symptoms of a Krebs cycle deficiency may include fatigue, muscle weakness and pain.

WARNINGS

WARNINGS: Keep out of reach of children. In case of overdose, get medical help or contact a Poison Control Center right away.

If pregnant or breast-feeding, ask a health professional before use.

Do not use if tamper evident seal is broken or missing.

DOSAGE AND ADMINISTRATION

DIRECTIONS: 10 drops orally, 3 times a day. Consult a physician for use in children under 12 years of age.

INACTIVE INGREDIENTS: Demineralized Water, 25% Ethanol

QUESTIONS

Distributed By:

SYNERGY FORMULAS, INC.

251 West Road

Camobello, SC 29322

PACKAGE LABEL

Synergy Formulas

Krebs Stimulator Plus

HOMEOPATHIC

2 FL OZ (60 ML)